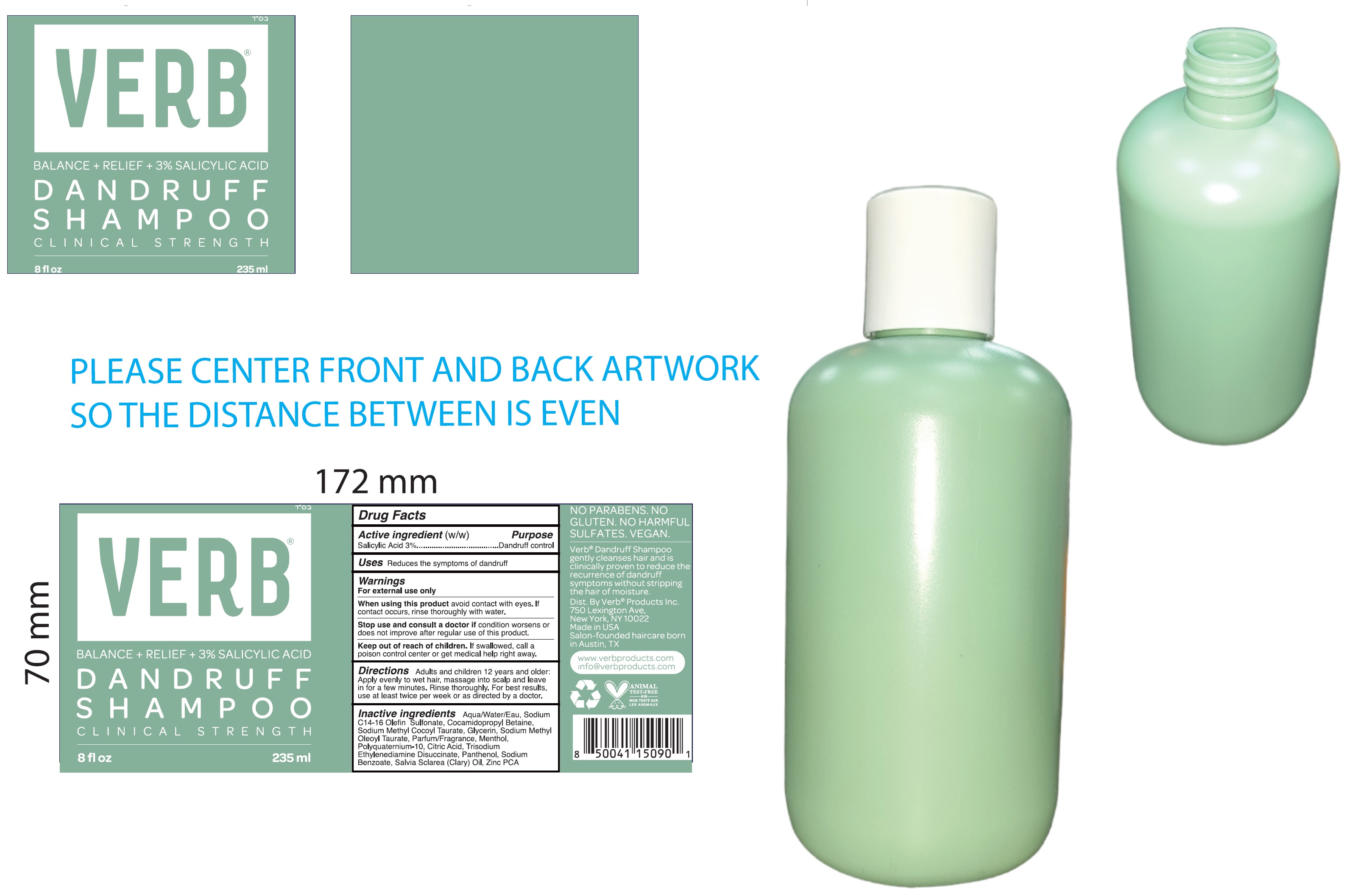 DRUG LABEL: VERB PRODUCTS Balance Relief Salicylic Acid Dandruff Clinical Strength
NDC: 84607-545 | Form: GEL
Manufacturer: Verb Products Inc.
Category: otc | Type: HUMAN OTC DRUG LABEL
Date: 20240903

ACTIVE INGREDIENTS: SALICYLIC ACID 30 mg/1 mL
INACTIVE INGREDIENTS: WATER; SODIUM C14-16 OLEFIN SULFONATE; COCAMIDOPROPYL BETAINE; SODIUM METHYL COCOYL TAURATE; GLYCERIN; SODIUM METHYL OLEOYL TAURATE; MENTHOL; CITRIC ACID MONOHYDRATE; TRISODIUM ETHYLENEDIAMINE DISUCCINATE; PANTHENOL; SODIUM BENZOATE; CLARY SAGE OIL; ZINC PIDOLATE

VERB PRODUCTS. Balance Relief 3% Salicylic Acid Dandruff Shampoo Clinical Strength

Active ingredient(w/w)

Salicylic Acid 3%

Purpose

Dandruff control

Uses

Reduces the symptoms of dandruff

Warnings

For external use only

When using this product

avoid contact with eyes. If contact occurs, rinse thoroughly with water.

Stop use and consult a doctor if

condition worsens or does not improve after regular use of this product.

Keep out of reach of children.

If swallowed, call a poison control center or get medical help right away.

Directions

Adults and children 12 years and older: Apply evenly to wet hair, massage into scalp and leave in for a few minutes. Rinse thoroughly. For best results, use at least twice per week or as directed by a doctor.

Inactive ingredients

Aqua/Water, Sodium C14-16 Olefin Sulfonate, Cocamidopropyl Betaine, Sodium Methyl Cocoyl Taurate, Glycerin, Sodium Methyl Oleoyl Taurate, Parfum/Fragrance, Menthol, Polyquaternium-10, Citric Acid, Trisodium Ethylenediamine Disuccinate, Panthenol, Sodium Benzoate, Salvia Sclarea (Clary) Oil, Zinc PCA